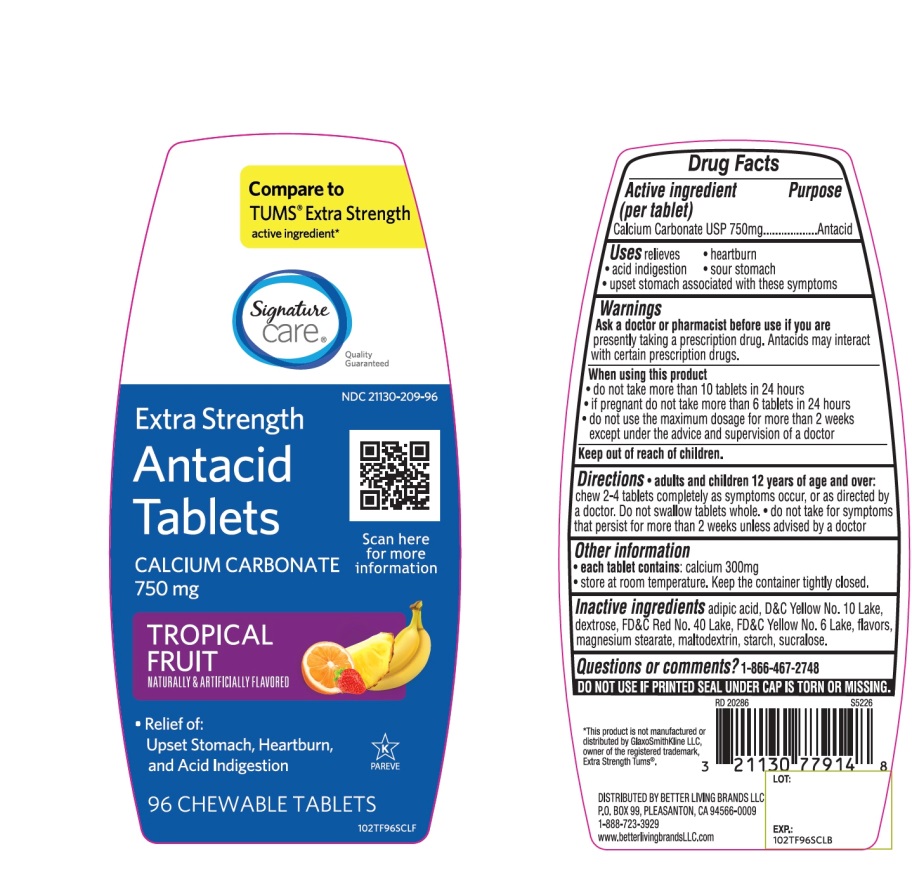 DRUG LABEL: Extra Strength
NDC: 21130-209 | Form: TABLET, CHEWABLE
Manufacturer: SAFEWAY
Category: otc | Type: HUMAN OTC DRUG LABEL
Date: 20251029

ACTIVE INGREDIENTS: CALCIUM CARBONATE 750 mg/1 1
INACTIVE INGREDIENTS: ADIPIC ACID; D&C YELLOW NO. 10; DEXTROSE, UNSPECIFIED FORM; FD&C RED NO. 40; FD&C YELLOW NO. 6; MAGNESIUM STEARATE; MALTODEXTRIN; STARCH, CORN; SUCRALOSE

Extra Strength Tropical Fruit Antacid 96 Tabs Drug Facts

Active ingredient (per tablet)

Calcium Carbonate USP 750mg

Purpose

Antacid

Uses

relieves

- heartburn
- acid indigestion
- sour stomach
- upset stomach associated with these symptoms

Warnings

Ask a doctor or pharmacist before use if you are

presently taking a prescription drug. Antacids may interact with certain prescription drug.

When using this product

- do not take more than 10 tablets in 24 hours
- if pregnant do not take more than 6 tablets in 24 hours
- do not use the maximum dosage for more than 2 weeks except under the advice and supervision of a doctor

Directions

- adults and children 12 years of age and over:chew 2-4 tablets as symptoms occur, or as directed by a doctor. Do not swallow tablets whole.
- do not take for symptoms that persist for more than 2 weeks unless advised by a doctor

Other information

- each tablet contains:calcium 300mg
- Store at room temperature. Keep the container tightly closed.

Inactive ingredients

adipic acid, D&C Yellow No. 10, dextrose, FD&C Red No. 40, FD &C Yellow No. 6, flavors, magnesium stearate, maltodextrin, starch, sucralose.

Questions or comments?

1-866-467-2748

SAFETY SEALED: DO NOT USE IF PRINTED SEAL UNDER CAP IS TORN OR MISSING.

Principal Display Panel

* Compare to the active ingredient Extra Strength Tums®

NDC# 21130-209-96

Extra Strength

Antacid Tablets

Calcium Carbonate 750 mg

Fast Relief of Upset Stomach, Heartburn and Acid Indigestion

Tropical Fruit

Naturally and Artificially Flavored

96 Chewable Tablets

GLUTEN FREE

Distributed by:

*This product is not manufactured or distributed by GlaxoSmithKline LLC, owner of the registered trademark, Extra Strength Tums®.